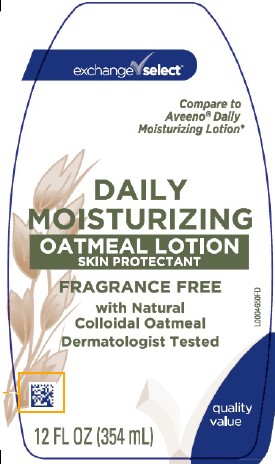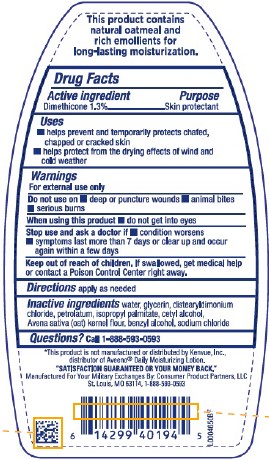 DRUG LABEL: Daily Moisturizing
NDC: 55301-619 | Form: LOTION
Manufacturer: Your Military Exchanges
Category: otc | Type: HUMAN OTC DRUG LABEL
Date: 20260212

ACTIVE INGREDIENTS: DIMETHICONE 1.3 kg/100 mL
INACTIVE INGREDIENTS: OATMEAL; BENZYL ALCOHOL; CETYL ALCOHOL; DISTEARYLDIMONIUM CHLORIDE; GLYCERIN; ISOPROPYL PALMITATE; PETROLATUM; SODIUM CHLORIDE; WATER

Exchange Select 619.003/619AC
Daily Moisturizing Lotion

Claims

This product contains natural oatmeal and rich emollients for long-lasting moisturization.

Active ingredient

Dimethicone 1.3%

Purpose

Skin protectant

Uses

- helps prevent and temporarily protects chafed, chapped or cracked skin
- helps protect from the drying effects of wind and cold weather

Warnings

For external use only

When using this product

- do not get in eyes

Stop use and ask a doctor if

- condition worsens
- symptoms last more than 7 days or clear up and occur again within a few days

Do not use on

- deep or punture wounds
- animal bites
- serious burns

Keep out of reach of children.

If swallowed, get medical help or contact a Poison Control Center right away.

Directions

apply as needed

Inactive ingredients

water, glycerin, distearyldimonium chloride, petrolatum, isopropyl palmitate, cetyl alcohol, Avena sativa (oat) kernel flour, benzyl alcohol, sodium chloride

Questions?

Call 1-888-593-0593

Disclaimer

*This product is not manufactured or distributed by Kenvue, Inc., distributor of Aveeno® Daily Moisturizing Lotion.

ADVERSE REACTION

"Satisfaction guaranteed or your money back."

Manufactured for Your Military Exchanges

By: Consumer Product Partners, LLC

St. Louis, MO 63114 1-888-593-0593

principal display panel

exchange select™

Compare to Aveeno® Daily Moisturizing Lotion*

DAILY MOISTURIZING

OATMEAL LOTION

SKIN PROTECTANT

FRAGRANCE FREE

with Natural Colloidal Oatmeal

Dermatologist Tested

quality value

12 FL OZ (354 mL)